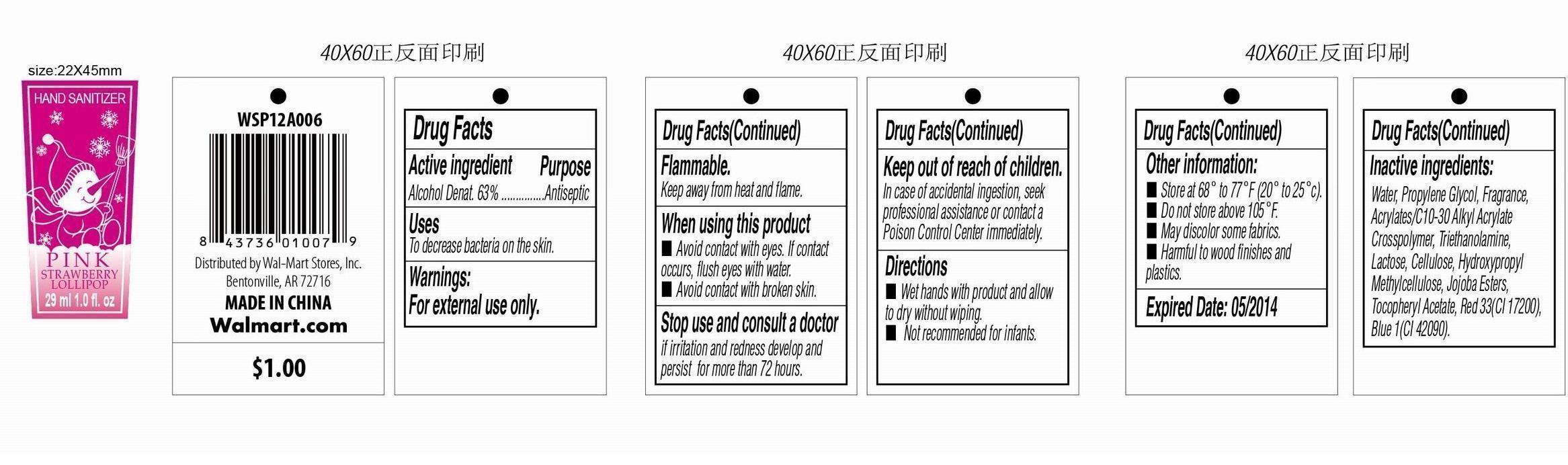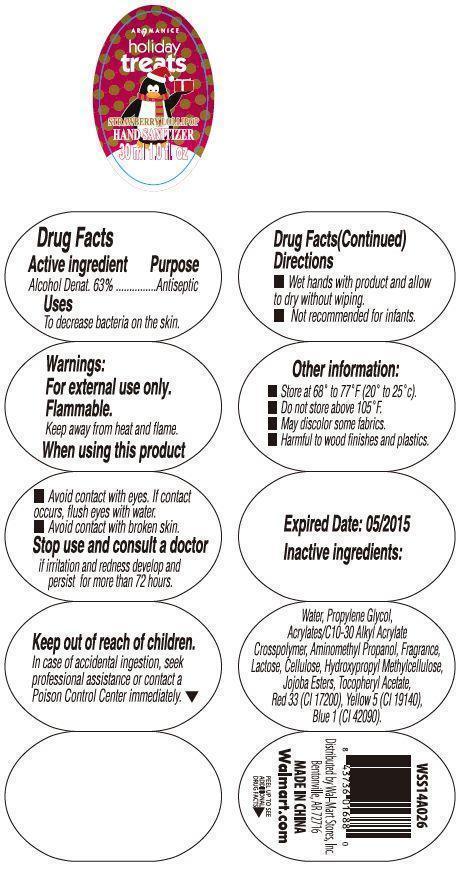 DRUG LABEL: Hand Sanitizer
NDC: 49035-211 | Form: LIQUID
Manufacturer: Wal-Mart Stores Inc.
Category: otc | Type: HUMAN OTC DRUG LABEL
Date: 20140502

ACTIVE INGREDIENTS: ALCOHOL 63 mL/100 mL
INACTIVE INGREDIENTS: Water; PROPYLENE GLYCOL; TROLAMINE; HYPROMELLOSES; CELLULOSE, MICROCRYSTALLINE; HYPROMELLOSE 2910 (5 MPA.S); FD&C BLUE NO. 1; D&C RED NO. 33

Drug Facts

Active Ingredient

Ethyl Alcohol 63%

Purpose

Anticeptic

Uses

To decrease bacteria on the skin.

Warning

For external use only.

Flammable.

Keep away from heat and flame.

When using this product

- Avoid contact with eyes. If contact occurs, flush eyes with water.
- Avoid contact with broken skin.

Stop use and consult a doctor if irritation and reness develop and persis for more than 72 hours.

Keep out of reach of children.

In case of accidental ingestion, seek professional assistance or contact a Poison Control Center immediately.

Directions

■ Wet hands with product and allow to dry without wiping.
■ Not recommended for infants.

Other Information

- Store at 68 o to 77 oF (20 o to 25 oc).
- Do not store above 105 oF.
- May discolor some fabrics.
- Harmful to wood finishes and plastics.

Inactive Ingredient

Alcohol Denat., Water, Propylene Glycol, Fragrance, Acrylates/C10-30 Alkyl Acrylate Crosspolymer, Triethanolamine, Lactose, Cellulose, Hydroxypropyl Methylcellulose, Jojoba Esters, Tocopheryl Acetate, Blue 1(CI 42090), Red 33(CI 17200), Red 4(CI 14700).